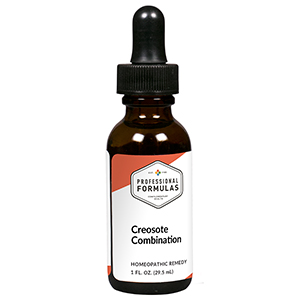 DRUG LABEL: Creosote Combination
NDC: 63083-9254 | Form: LIQUID
Manufacturer: Professional Complementary Health Formulas
Category: homeopathic | Type: HUMAN OTC DRUG LABEL
Date: 20190815

ACTIVE INGREDIENTS: ACONITUM NAPELLUS WHOLE 4 [hp_X]/29.5 mL; AMARYLLIS BELLADONNA WHOLE 4 [hp_X]/29.5 mL; BRYONIA ALBA ROOT 4 [hp_X]/29.5 mL; HYOSCYAMUS NIGER 4 [hp_X]/29.5 mL; IPECAC 4 [hp_X]/29.5 mL; LOBELIA INFLATA WHOLE 4 [hp_X]/29.5 mL; LOBARIA PULMONARIA 4 [hp_X]/29.5 mL; PHOSPHORUS 5 [hp_X]/29.5 mL; ANTIMONY POTASSIUM TARTRATE 6 [hp_X]/29.5 mL; WOOD CREOSOTE 6 [hp_X]/29.5 mL; SILICON DIOXIDE 6 [hp_X]/29.5 mL; HUMAN SPUTUM, BORDETELLA PERTUSSIS INFECTED 30 [hp_X]/29.5 mL; CLOSTRIDIUM TETANI TOXOID ANTIGEN (FORMALDEHYDE INACTIVATED) 30 [hp_X]/29.5 mL
INACTIVE INGREDIENTS: ALCOHOL; WATER

R254

ACTIVE INGREDIENTS

Aconitum napellus 4X
Belladonna 4X
Bryonia 4X
Hyoscyamus niger 4X
Ipecacuanha 4X
Lobelia inflata 4X
Sticta pulmonaria 4X
Phosphorus 5X
Antimonium tartaricum 6X
Kreosotum 6X
Silicea 6X
Pertussinum 30X
Tetanus 30X

QUESTIONS

Professional Formulas

PO Box 2034 Lake Oswego, OR 97035

INDICATIONS

For the temporary relief of coughing, wheezing, chills, sweats, fatigue, minor aches and pains, and irritation, tenderness or mild pain in the nose or throat.*

PURPOSE

*Claims based on traditional homeopathic practice, not accepted medical evidence. Not FDA evaluated.

WARNINGS

If symptoms do not improve or are accompanied by fever, consult a doctor. Keep out of the reach of children. In case of overdose, get medical help or contact a poison control center right away. If pregnant or breastfeeding, ask a healthcare professional before use.

Keep out of the reach of children.

PREGNANCY OR BREAST FEEDING

If pregnant or breastfeeding, ask a healthcare professional before use.

DIRECTIONS

Place drops under tongue 30 minutes before/after meals. Adults and children 12 years and over: Take 10 drops up to 3 times per day. Consult a physician for use in children under 12 years of age.

OTHER INFORMATION

Tamper resistant. If seal is broken, do not use. After opening, close container tightly and store at room temperature away from heat.

INACTIVE INGREDIENTS

40% ethanol, purified water.

LABEL

Est 1985

Professional Formulas

Complementary Health

Creosote Combination

Homeopathic Remedy

1 FL. OZ. (29.5 mL)